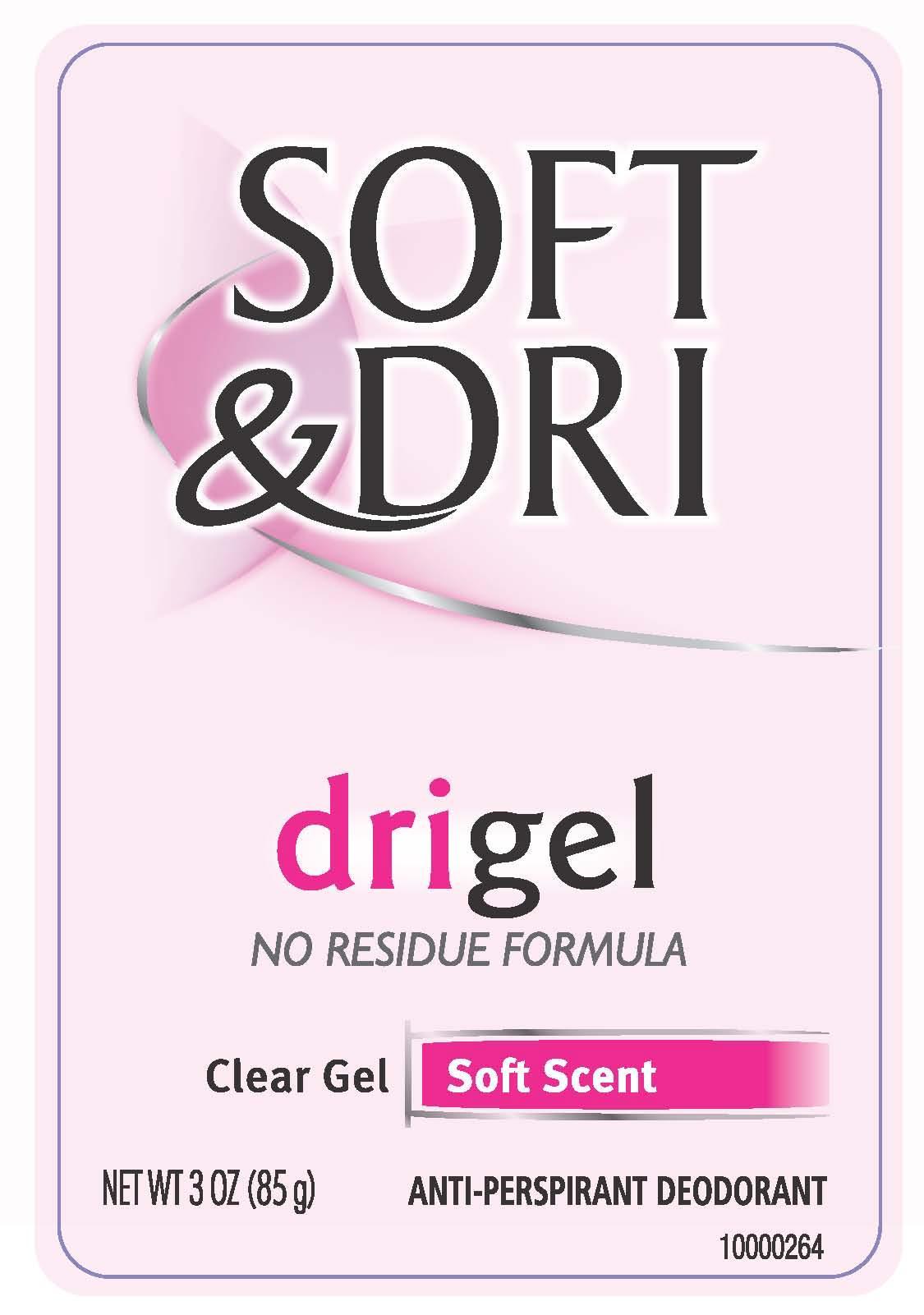 DRUG LABEL: Soft and Dri Dri Gel
NDC: 51815-217 | Form: STICK
Manufacturer: VVF Illinois Services
Category: otc | Type: HUMAN OTC DRUG LABEL
Date: 20140227

ACTIVE INGREDIENTS: ALUMINUM ZIRCONIUM OCTACHLOROHYDREX GLY 85 g/85 g
INACTIVE INGREDIENTS: WATER; ALCOHOL; CYCLOMETHICONE; PROPYLENE GLYCOL; DIMETHICONE; TRISILOXANE; CALCIUM CHLORIDE; PEG/PPG-18/18 DIMETHICONE

Soft and Dri Dri Gel Soft Scent

Active Ingredient

Aluminum Zirconium Octachlorohydrex GLY 16.4%

Purpose

Antiperspirant

Warnings

For external use only

Do not use on broken skin

Stop use and ask a doctor if rash or irritation occurs

Keep out of reach of children.

If swallowed, get medical help or contact poison control center right away

Ask doctor before use if you have kidney disease

Use

Reduces underarm perspiration

Inactive Ingredients

Water, alcohol

denat., cyclomethicone, propylene glycol,

dimethicone, trisiloxane, calcium chloride,

PEG/PPG-18/18 dimethicone, fragrance

For questions or the latest product news,

visit www.softndri.com

Directions

Apply to underarms only